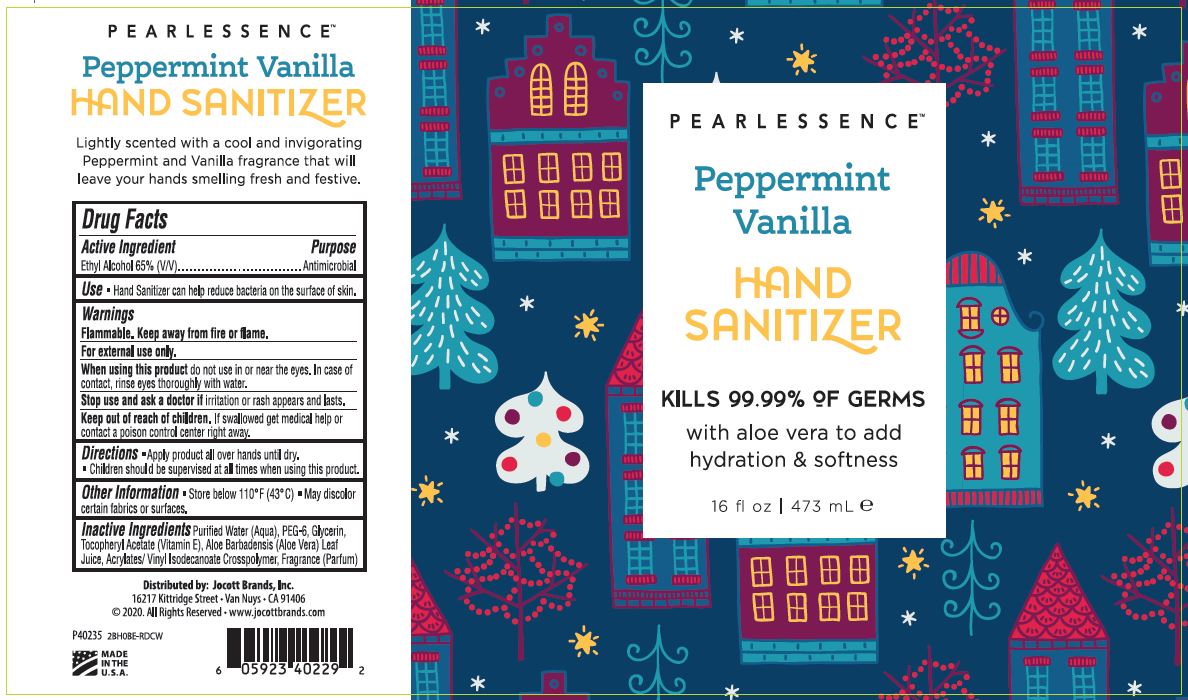 DRUG LABEL: PEARLESSENCE HAND SANITIZER
NDC: 78902-122 | Form: GEL
Manufacturer: Jocott Brands, Inc.
Category: otc | Type: HUMAN OTC DRUG LABEL
Date: 20201003

ACTIVE INGREDIENTS: ALCOHOL 65 mL/100 mL
INACTIVE INGREDIENTS: WATER; POLYETHYLENE GLYCOL 300; GLYCERIN; .ALPHA.-TOCOPHEROL ACETATE; ALOE VERA LEAF; ACRYLATES/VINYL ISODECANOATE CROSSPOLYMER (10000 MPA.S NEUTRALIZED AT 0.5%)

PEARLESSENCE HAND SANITIZER GEL - WITH ALOE VERA - PEPPERMINT VANILLA - 65% Ethyl Alcohol

ACTIVE INGREDIENT

ETHYL ALCOHOL 65% (V/V)

PURPOSE

ANTIMICROBIAL

USE

- HAND SANITIZER CAN HELP REDUCE BACTERIA ON THE SURFACE OF SKIN.

WARNINGS

FLAMMABLE. KEEP AWAY FROM FIRE OR FLAME.

FOR EXTERNAL USE ONLY.

WHEN USING THIS PRODUCT DO NOT USE IN OR NEAR THE EYES. IN CASE OF CONTACT, RINSE EYES THOROUGHLY WITH WATER.

STOP USE AND ASK A DOCTOR IF IRRITATION OR RASH APPEARS AND LASTS.

KEEP OUT OF REACH OF CHILDREN. IF SWALLOWED GET MEDICAL HELP OR CONTACT A POISON CONTROL CENTER RIGHT AWAY.

DIRECTIONS

- APPLY PRODUCT ALL OVER HANDS UNTIL DRY.
- CHILDREN SHOULD BE SUPERVISED AT ALL TIMES WHEN USING THIS PRODUCT.

OTHER INFORMATION

- STORE BELOW 110°F (43°C)
- MAY DISCOLOR CERTAIN FABRICS OR SURFACES

INACTIVE INGREDIENTS

Purified Water (Aqua), PEG-6, Glycerin, Tocopheryl Acetate (Vitamin E), Aloe Barbadensis (Aloe Vera) Leaf Juice, Acrylates/Vinyl Isodecanoate Crosspolymer, Fragrance (Parfum)